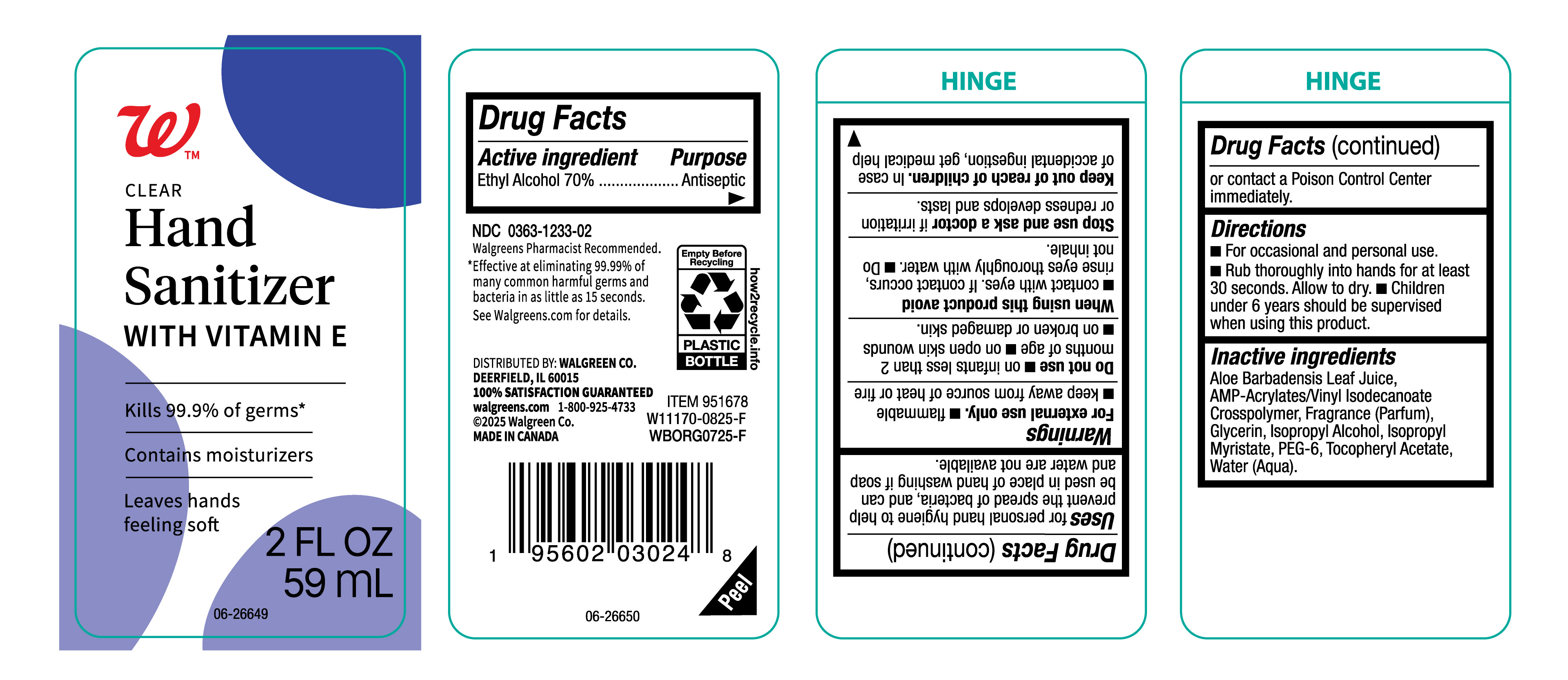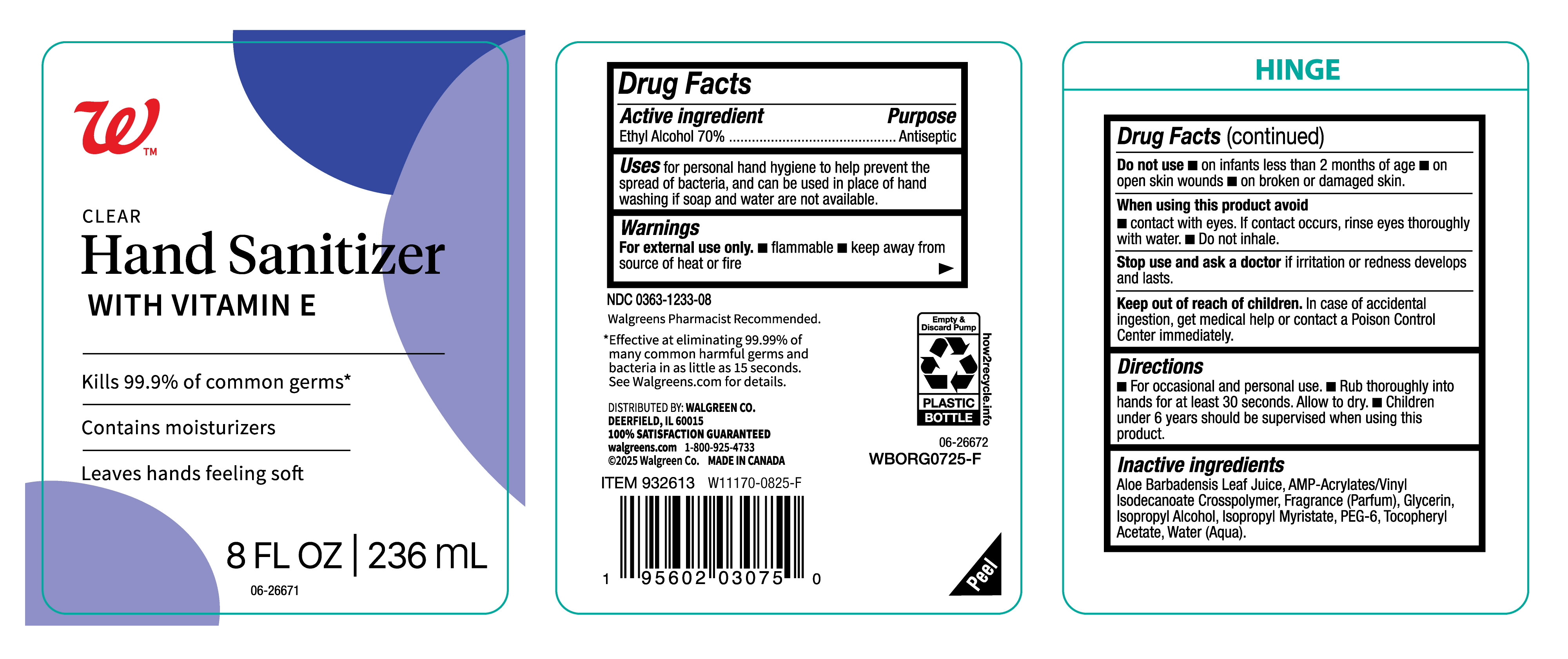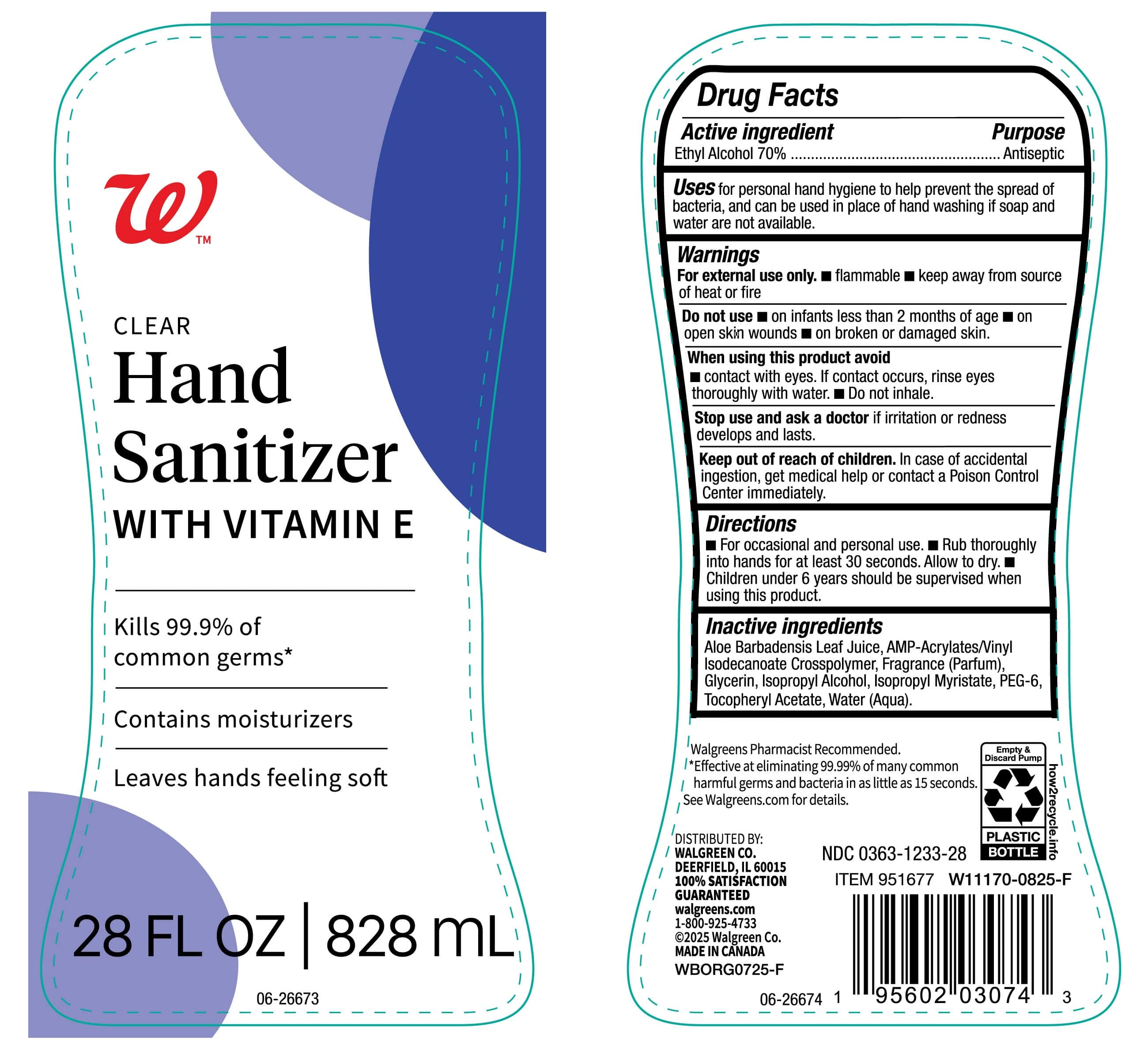 DRUG LABEL: Walgreens
NDC: 0363-1233 | Form: GEL
Manufacturer: Walgreens
Category: otc | Type: HUMAN OTC DRUG LABEL
Date: 20250901

ACTIVE INGREDIENTS: ALCOHOL 700 mg/1 mL
INACTIVE INGREDIENTS: GLYCERIN; ISOPROPYL MYRISTATE; ALOE VERA LEAF; FRAGRANCE CLEAN ORC0600327; ISOPROPYL ALCOHOL; PEG-6; ACRYLATES/VINYL ISODECANOATE CROSSPOLYMER (10000 MPA.S NEUTRALIZED AT 0.5%); WATER; .ALPHA.-TOCOPHEROL ACETATE

Walgreens Hand sanitizer-0363-1233

ACTIVE INGREDIENT

Ethyl alcohol 70%

Purpose

Antiseptic

Uses

For personal hand hygiene to help prevent the spread of bacteria, and can be used in place of hand washing if soap and water are not available.

Warnings

For external use only..

- Flammable
- keep away from source of heat or fire

Do not use

- on infants less than 2 months of age.
- on open skin wounds
- on broken or damaged skin

When using this product avoid

- contact with eyes. if contact occurs, rinse eyes thoroughly with water.
- Do not inhale.

Stop use and ask a doctor

if irritation or redness develops and lasts.

Keep out of reach of children.

In case of accidental ingestion, get medical help or contact a Poison Control Center Immediately.

Directions

- For occassional and personal use.
- Rub thoroughly into hands for at least 30 seconds. Allow to dry.
- Children under 6 years should be supervised when using this product.

Inactive Ingredients

Aloe Barbadensis Leaf Juice, AMP-Acrylates/Vinyl Isodecanate Crossploymer, Fragrance (Parfum), Glycerin, Isopropyl Alcohol, Isopropyl Myristate, PEG-6, Tocopheryl Acetate, Water (Aqua).